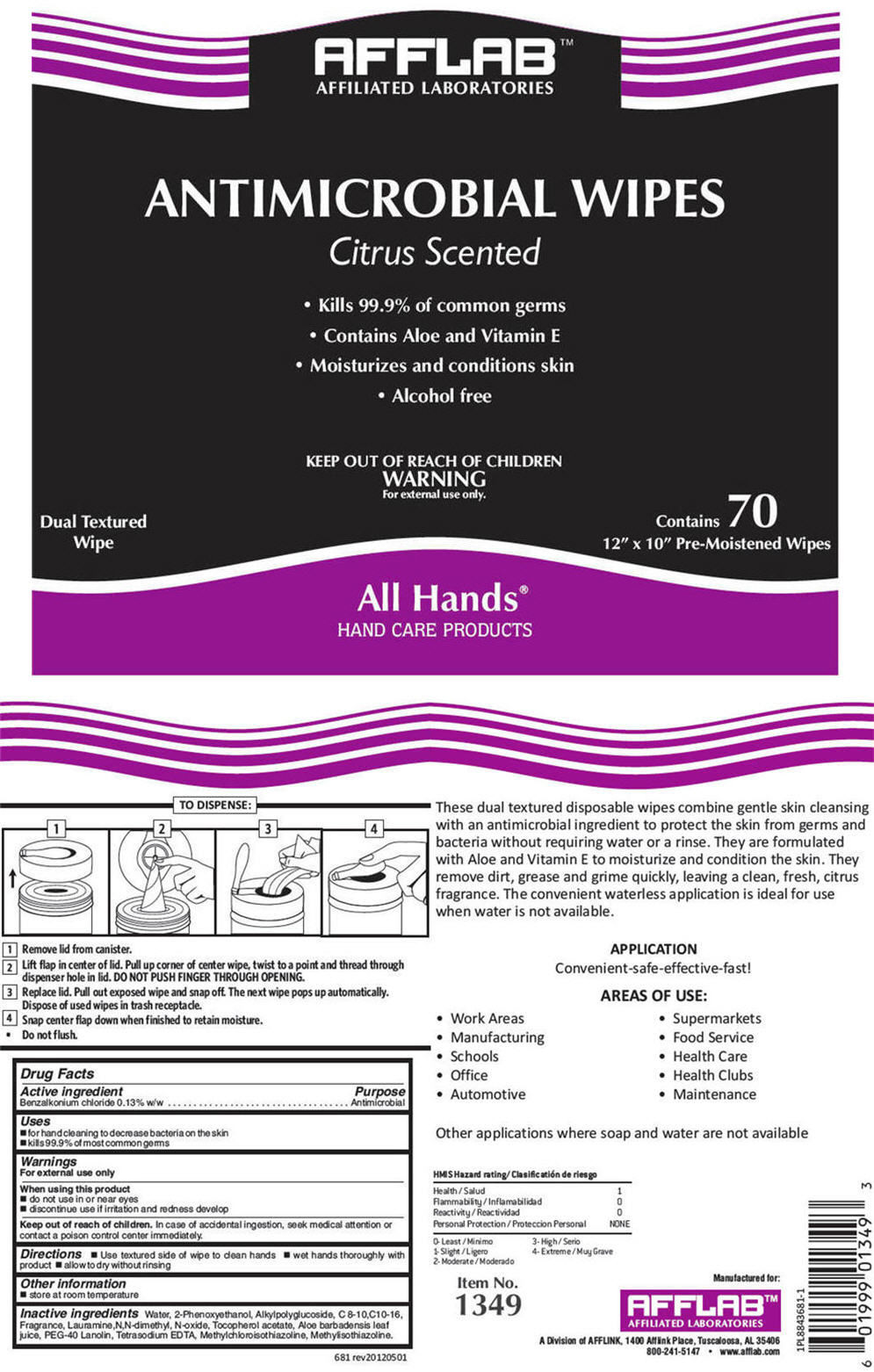 DRUG LABEL: Antimicrobial Wipes Citrus Scented
NDC: 54057-681 | Form: CLOTH
Manufacturer: AFFLABS, Affiliated Laboratories, A Division of AFFLINK
Category: otc | Type: HUMAN OTC DRUG LABEL
Date: 20121107

ACTIVE INGREDIENTS: BENZALKONIUM CHLORIDE 0.01417 g/1 1
INACTIVE INGREDIENTS: Water; phenoxyethanol; DECYL GLUCOSIDE; LAURAMINE OXIDE; .Alpha.-Tocopherol Acetate; Aloe Vera Leaf; Edetate Sodium; Methylchloroisothiazolinone; Methylisothiazolinone

Antimicrobial Wipes Citrus Scented

Drug Facts

Active ingredient

Benzalkonium chloride 0.13% w/w

Purpose

Antimicrobial

Uses

- for hand cleaning to decrease bacteria on the skin
- kills 99.9% of most common germs

Warnings

For external use only

When using this product

- do not use in or near eyes
- discontinue use if irritation and redness develop

Keep out of reach of children. In case of accidental ingestion, seek medical attention or contact a poison control center immediately.

Directions

- Use textured side of wipe to clean hands
- wet hands thoroughly with product
- allow to dry without rinsing

Other information

- store at room temperature

Inactive ingredients

Water, 2-Phenoxyethanol, Alkylpolyglucoside, C 8-10,C10-16, Fragrance, Lauramine,N,N-dimethyl, N-oxide, Tocopherol acetate, Aloe barbadensis leaf juice, PEG-40 Lanolin, Tetrasodium EDTA, Methylchloroisothiazoline, Methylisothiazoline.

Manufactured for:
AFFLAB™
AFFILIATED LABORATORIES
A Division of AFFLINK, 1400 Afflink Place, Tuscaloosa, AL 35406

PRINCIPAL DISPLAY PANE - Canister Label

AFFLAB™
AFFILIATED LABORATORIES

ANTIMICROBIAL WIPES

Citrus Scented

- Kills 99.9% of common germs
- Contains Aloe and Vitamin E
- Moisturizes and conditions skin
- Alcohol free

KEEP OUT OF REACH OF CHILDREN
WARNING
For external use only.

Dual Textured
Wipe

Contains 70
12″ x 10″ Pre-Moistened Wipes

All Hands®
HAND CARE PRODUCTS